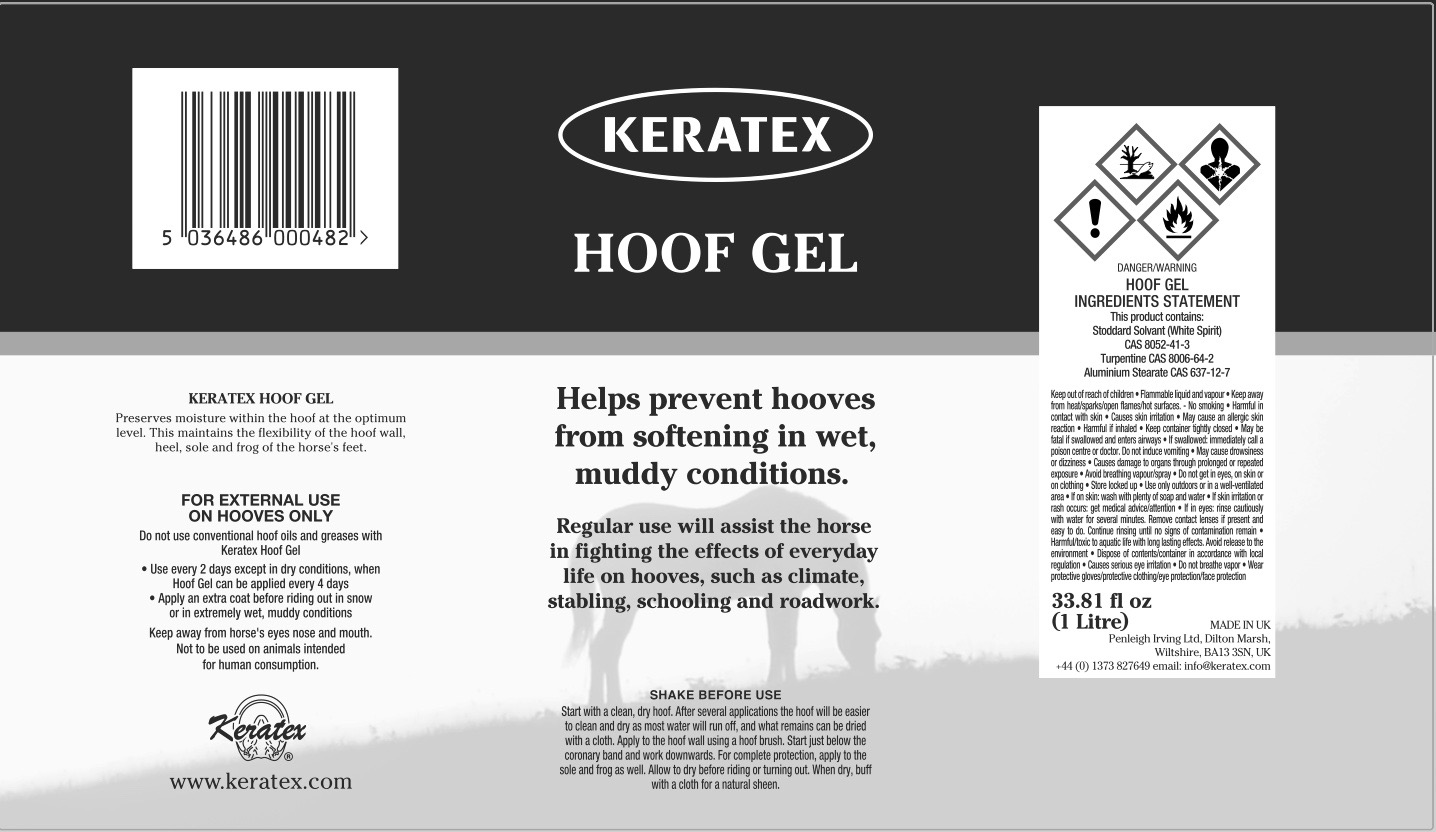 DRUG LABEL: Keratex
NDC: 27426-020 | Form: Liquid
Manufacturer: Penleigh Irving Ltd
Category: animal | Type: OTC ANIMAL DRUG LABEL
Date: 20190102

ACTIVE INGREDIENTS: ALUMINUM STEARATE 2.5 g/1 mL
INACTIVE INGREDIENTS: TURPENTINE; WHITE SPIRIT TYPE 1

SAFE HANDLING WARNING

Keep away from children. Flammable liquid and vapour. Keep away from heat/sparks/open flames/hot surfaces. No smoking. Harmful in contact with skin. Causes skin irriation. May cause an allergic skin reaction. Harmful if inhaled. Keep container tightly closed. May be fatal if swallowed and enters airways. If swallowed: immediately call a poison centre or doctor. Do not induce vomiting. May cause drowsiness or dizziness. Causes damage to organs through prolonged or repeated exposure. Avoid breathing vapour/spray. Do not get in eyes, or skin or on clothing. Store locked up. Use only outdoors or in a well-ventilated area. If on skin: Wash with plenty of soap and water. If skin irritation or rash occurs: Get medical advice/attention. If in eyes: Rinse cautiously with water for several minutes. Remove contact lenses if present and easy to do. Continue rinsing until no signs of contamination remain. Harmful/toxic to acquatic life with long lasting effects. Avoid release to the environment. Dispose of contents/container in accordance with local regulation. Causes serious eye irritation. Do not breath vapor. Wear protective gloves/protective clothing/eye protection/face protection.

PACKAGE LABEL

Keratex Hoof Gel

Helps prevent hooves from softening in wet, muddy conditions. Regular use will assist the horse in fighting the effects of everyday life on hooves, such as climate, stabling, schooling and roadwork.

Shake Before Use. Start with a clean, dry hoof. After several applications the hoof will be easier to clean and dry as most water will run off, and what remains can be dried with a cloth. Apply to the hoof wall using a hoof brush. Start just below the coronary band and work downwards. For complete protection, apply to the sole and frog as well. Allow to dry before riding or turning out. When dry, buff with a cloth for a natural sheen.

Keratex Hoof Gel preserves moisture within the hoof at the optimum level. This maintains the flexibility of the hoof wall, heel, sole and frog of the horse’s feet.

Do not use conventional hoof oils and greases with Keratex Hoof Gel. Use every 2 days except in dry conditions, when Hoof Gel can be applied every 4 days. Apply an extra coat before riding out in snow or in extremely wet, muddy conditions.

For External Use on Hooves Only.

Keep away from horse's eyes, nose and mouth. Not to be used on animals intended for human consumption.

Hoof Gel Ingredients Statement. This product contains: Stoddard Solvent (White Spirit) CAS 8052-41-3. Turpentine CAS 8006-64-2. Aluminium Stearate CAS 637-12-7.

33.81 fl oz (1 Litre)

Made in UK

Penleigh Irving Ltd.

Dilton Marsh, Wiltshire, BK13 3SN, UK

+44 (0) 1373 827649 email: info@keratex.com

www.keratex.com